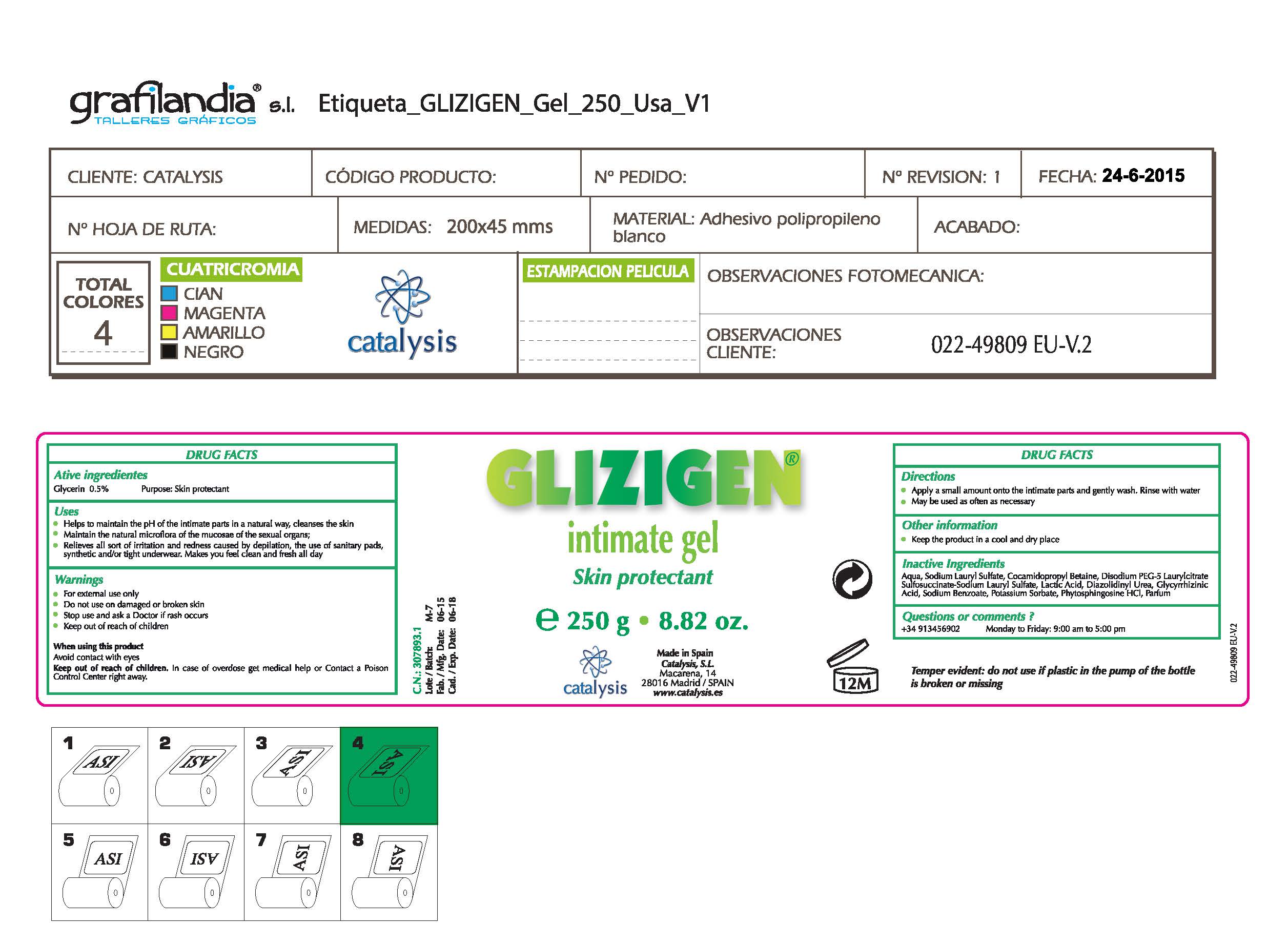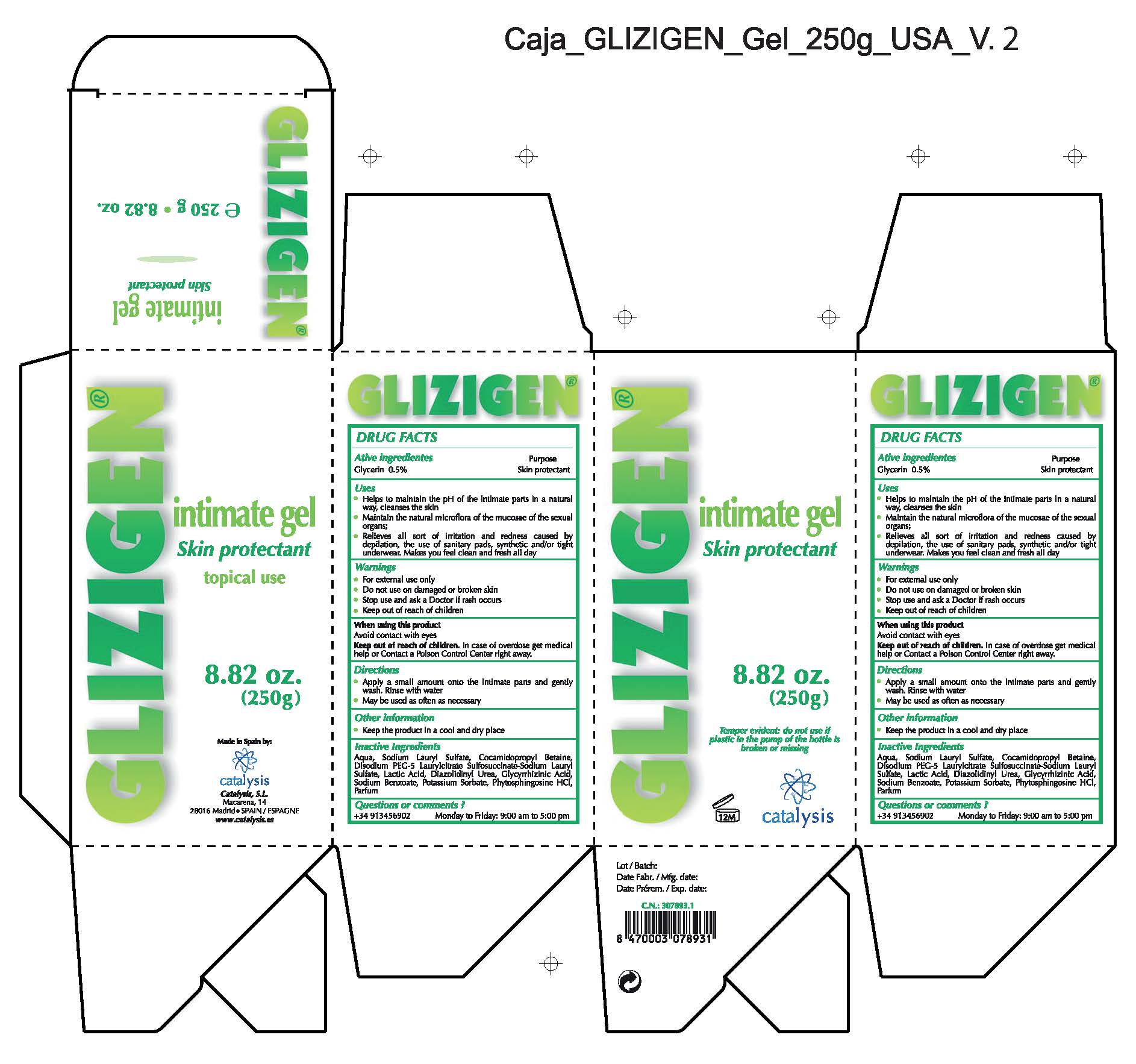 DRUG LABEL: Glizigen Gel Intimate
NDC: 64539-017 | Form: GEL
Manufacturer: Catalysis, SL
Category: otc | Type: HUMAN OTC DRUG LABEL
Date: 20180318

ACTIVE INGREDIENTS: GLYCERIN 0.5 mg/1 mL
INACTIVE INGREDIENTS: COCAMIDOPROPYL BETAINE 12 mg/1 mL; GLYCYRRHIZIN 0.1 mg/1 mL; POTASSIUM SORBATE 0.1 mg/1 mL; SODIUM LAURYL SULFATE 20 mg/1 mL; DISODIUM LAURETH SULFOSUCCINATE 3 mg/1 mL; LACTIC ACID 0.36 mg/1 mL; DIAZOLIDINYL UREA 0.3 mg/1 mL; SODIUM BENZOATE 0.1 mg/1 mL; PHYTOSPHINGOSINE 0.01 mg/1 mL; WATER 100 mg/1 mL

Glizigen Intimate Gel

ACTIVE INGREDIENT

Glycerin 0.5%...................Skin Protectant

- Stop use and ask a doctor if rash occurs
- Children under 6 months: ask a doctor

- Keep out of reach of children

WARNINGS

- For external use only.
- Do not use on damaged or broken skin.
- When using this product keep our of the eyes. Rinse with water to remove.
- Stop use and ask a doctor if rash occurs.
- Keep out of reach of children
- Children under 6 months: as a doctor.

INDICATIONS AND USAGE

- Apply a small amount the intimate parts and gently wash. Rinse with water
- Maybe used as often as necessary

PURPOSE

- Apply a small amount the intimate parts and gently wash. Rinse with water
- Maybe used as often as necessary

- Stop use and ask a doctor if rash occurs
- Children under 6 months: ask a doctor

QUESTIONS

+ 34 913456902 Monday to Friday: 9:00 am to 5:00 pm

OTHER SAFETY INFORMATION

- keep the product in a cool and dry place

DOSAGE AND ADMINISTRATION

- Apply a small amount the intimate parts and gently wash. Rinse with water
- Maybe used as often as necessary

INACTIVE INGREDIENT

Water, Sodium Lauryl Sulfate, Cocamidopropyl Betaine, Disodium Laureth Sulfosuccinate, Lactic Acid, Diazolidinyl Urea, Glycyrrhizinic,Acid, Sodium Benzoate, Potassium Sorbate, Phytosphingosine HCl, Parfum